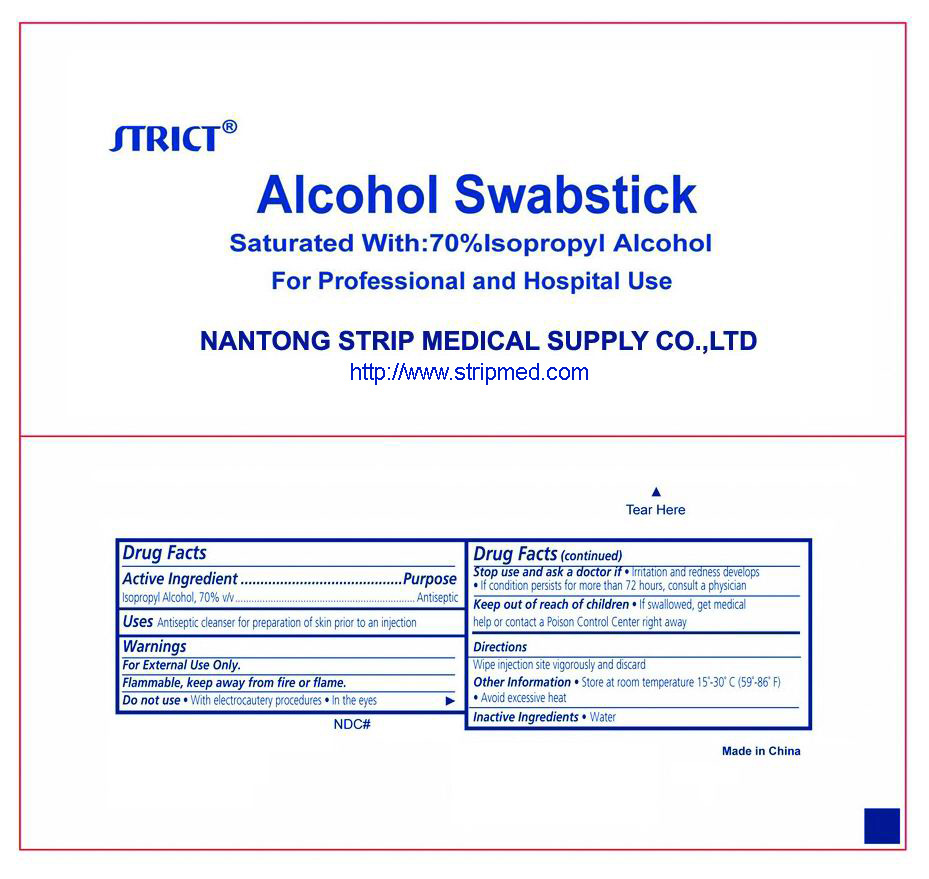 DRUG LABEL: Alcohol
NDC: 35617-396 | Form: SWAB
Manufacturer: NANTONG STRIP MEDICAL SUPPLY CO.,LTD.
Category: otc | Type: HUMAN OTC DRUG LABEL
Date: 20110705

ACTIVE INGREDIENTS: ISOPROPYL ALCOHOL 0.7 mL/1 1
INACTIVE INGREDIENTS: WATER 0.3 mL/1 1

Drug Facts Alcohol Swabstick

Active Ingredient

Isopropyl Alcohol 70%

Purpose

Antiseptic

Use

Antiseptic cheanser for preparation of the skin prior to an injection

Warnings

For external use only. Flammable, keep away from fire or flame
DO not use with electrocautery procedures. DO not use In the eyes.
Stop Use and ask a doctor if irritation and redness develops .If condition persists for more than 72hours, consult a physician

KEEP OUT OF REACH OF CHILDREN

Keep this and all drugs out of reach of children. In case of accidental ingestion seek professional assistance or contact a Poison Control Center immediately.

Directions

Wipe injection site vigorously and discard.

OTHER SAFETY INFORMATION

Store at room temperature, 59º-86ºF(15º-30℃). Avoid excessive heat

Inactive Ingredients

Inactive Ingredients: Water